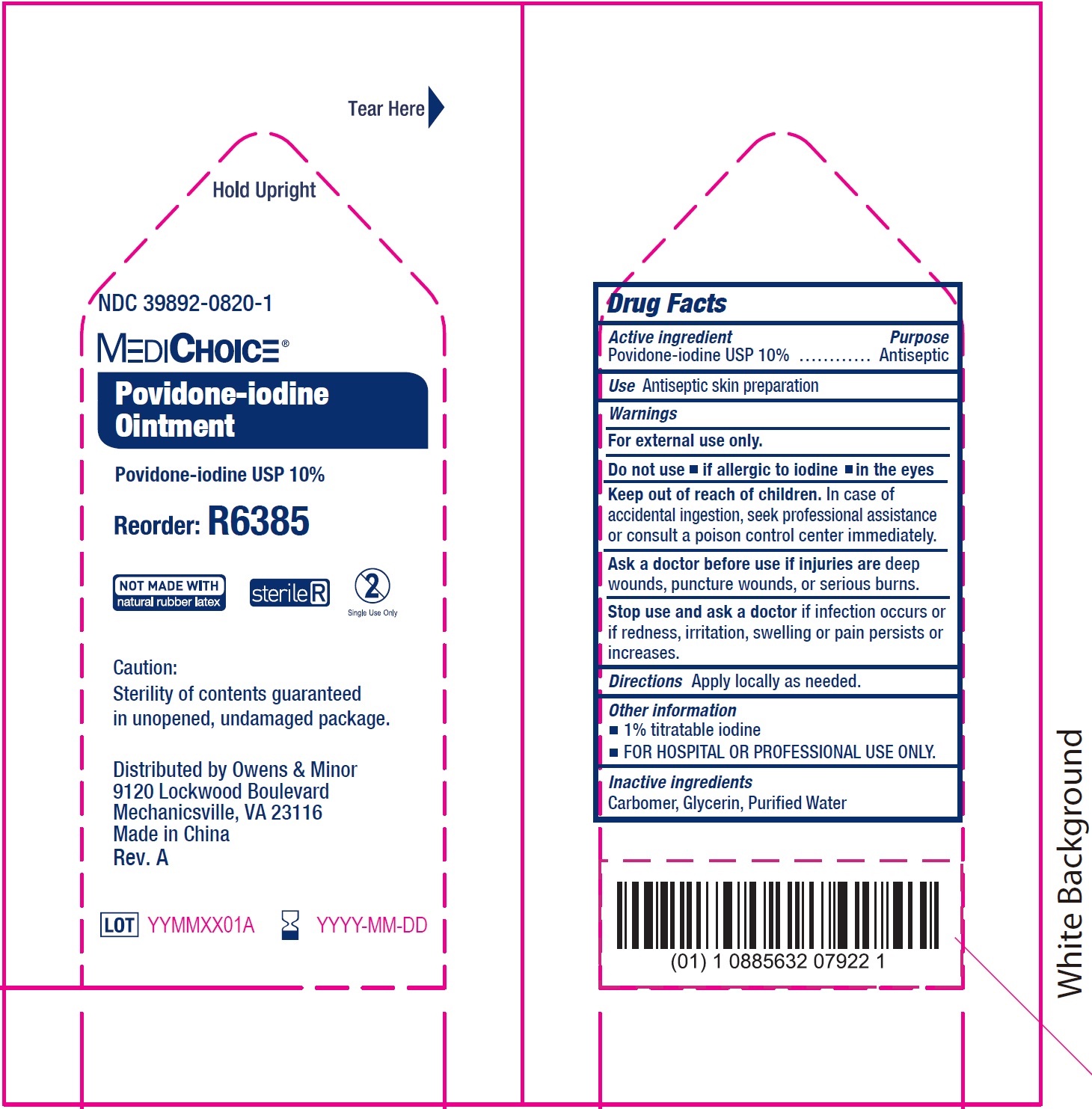 DRUG LABEL: MediChoice Povidone-Iodine
NDC: 39892-0820 | Form: OINTMENT
Manufacturer: O&M HALYARD, INC.
Category: otc | Type: HUMAN OTC DRUG LABEL
Date: 20251009

ACTIVE INGREDIENTS: POVIDONE-IODINE 100 mg/1 g
INACTIVE INGREDIENTS: CARBOXYPOLYMETHYLENE; GLYCERIN; WATER

MediChoice Povidone-Iodine Ointment

Active ingredient

Povidone-iodine USP 10%

Purpose

Antiseptic

Use

Antiseptic skin preparation

Warnings

For external use only.

Do not use

- if allergic to iodine
- in the eyes

Keep out of reach of children.

In case of accidental ingestion, seek professional assistance or consult a poison control center immediately.

Ask a doctor before use

if injuries are deep wounds, puncture wounds, or serious burns.

Stop use and ask a doctor

if infection occurs or if redness, irritation, swelling or pain persists or increases.

Directions

Apply locally as needed.

Other information

- 1% titratable iodine
- FOR HOSPITAL OR PROFESSIONAL USE ONLY.

Inactive ingredients

Carbomer, Glycerin, Purified Water